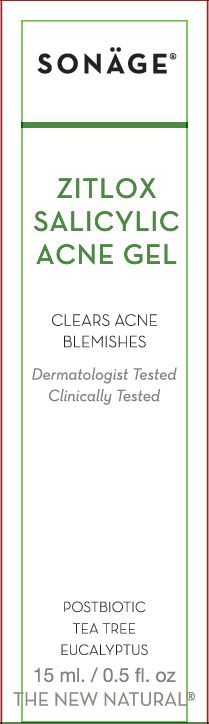 DRUG LABEL: Zitlox Salicylic Acne
NDC: 69546-201 | Form: GEL
Manufacturer: ASA Universal Inc. dba: SONAGE
Category: otc | Type: HUMAN OTC DRUG LABEL
Date: 20250106

ACTIVE INGREDIENTS: SALICYLIC ACID 1.5 g/100 mL
INACTIVE INGREDIENTS: BENZYL ALCOHOL; SAFFLOWER OIL; COCONUT OIL; DEHYDROACETIC ACID; DIATOMACEOUS EARTH; EUCALYPTUS OIL; GLYCERIN; SUNFLOWER OIL; TEA TREE OIL; AZADIRACHTA INDICA SEED OIL; PEPPERMINT OIL; OLIVE OIL; AMMONIUM ACRYLOYLDIMETHYLTAURATE, DIMETHYLACRYLAMIDE, LAURYL METHACRYLATE AND LAURETH-4 METHACRYLATE COPOLYMER, TRIMETHYLOLPROPANE TRIACRYLATE CROSSLINKED (45000 MPA.S); SODIUM HYDROXIDE; TERT-BUTYL ALCOHOL; WATER; XANTHAN GUM

Zitlox Salicylic Acne Gel

Active Ingredient

Salicylic Acid 1.5%

Purpose

Acne Treatment

Uses

- clears acne blemishes and allows skin to heal
- helps prevent new acne blemishes from forming

Warnings

For external use only

When using this product

Skin irritation and dryness is more likely to occur if you use another topical acne medication at the same time. If irritation occurs, only use one topical acne medication at a time

Keep out of reach of children.

If swallowed, get medical help or contact a Poison Control Center right away.

Directions

- clean the skin thoroughly before applying this product.
- cover the entire affected area with a thin layer one to three time daily
- because excessive drying of the skin may occur, start with one application daily, then gradually increase to two or three times daily if needed or as directed by doctor
- if bothersome dryness or peeling occurs, reduce application to once a day or every other day

Inactive Ingredients

bacillus ferment filtrate extract (postbiotic), benzyl alcohol, carthamnus tinctorius (safflower) oil, cocos nucifera (coconut) oil, dehydroacetic acid, diatomaceous earth, eucalyptus globulus leaf oil, glycerin, helianthus annuus (sunflower) seed oil, melaleuca alternifolia (tea tree) leaf oil, melia azadirachta (neem) seed oil, mentha piperita (peppermint) oil, olea europaea (olive) fruit oil, polyacrylate crosspolymer-6, sodium hydroxide, t-butyl alcohol, water, xanthan gum

Principal Display Panel

SONÄGE®

ZITLOX
SALICYLIC
ACNE GEL
CLEARS ACNE
BLEMISHES

Dermatologist Tested
Clinically Tested
POSTBIOTIC
TEA TREE
EUCALYPTUS
15 ml. / 0.5 fl. oz.
THE NEW NATURAL®

Dist. by/par Sonäge, Santa Monica,
CA 90405 U.S.A
sonage.com

Label